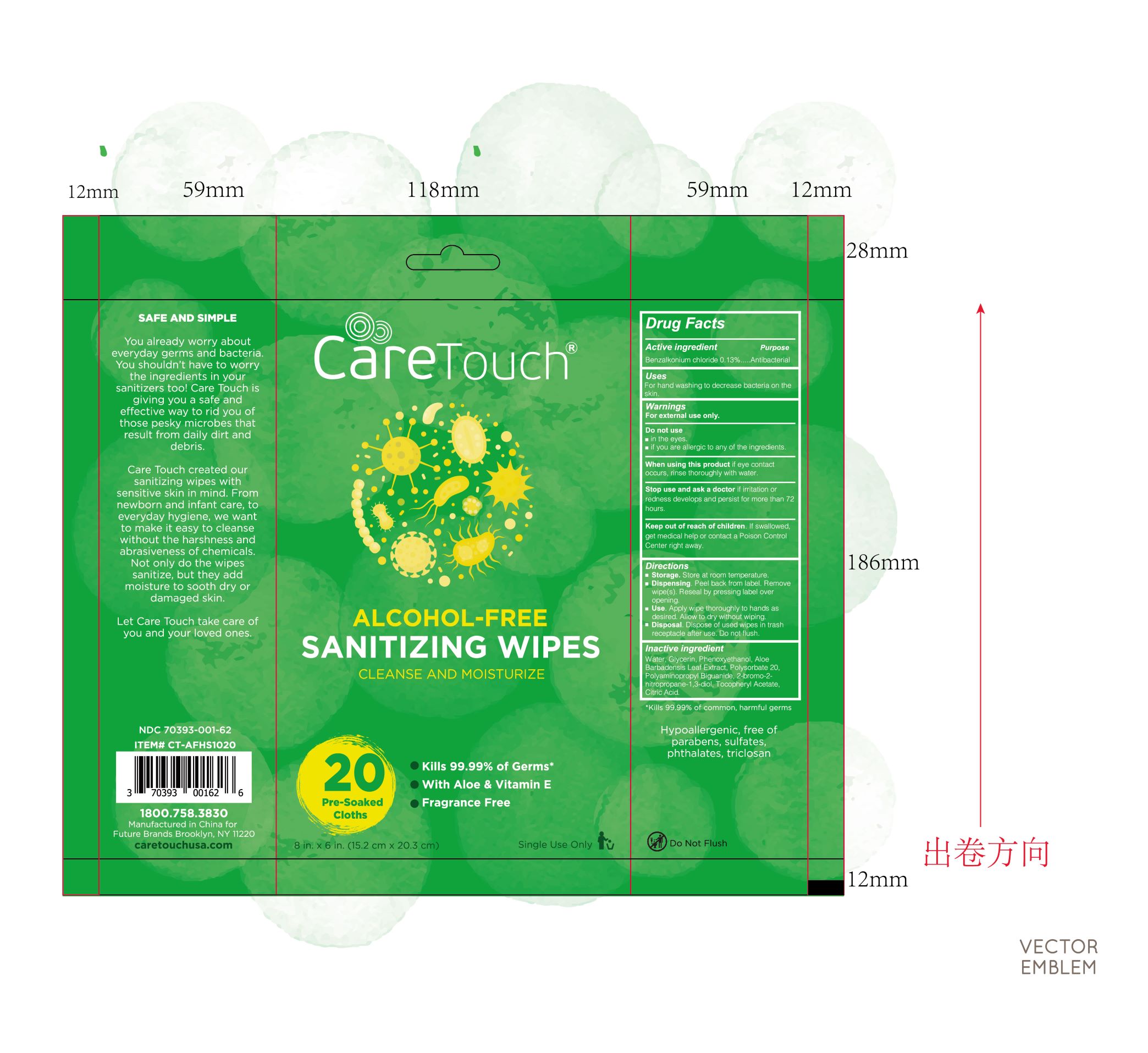 DRUG LABEL: ALCOHOL-FREE SANITIZING WIPES
NDC: 40562-010 | Form: CLOTH
Manufacturer: Anhui Hanbon Daily Chemical Co., Ltd.
Category: otc | Type: HUMAN OTC DRUG LABEL
Date: 20220123

ACTIVE INGREDIENTS: BENZALKONIUM CHLORIDE 0.13 mg/100 mL
INACTIVE INGREDIENTS: ALOE VERA LEAF; BRONOPOL; POLYSORBATE 20; POLYAMINOPROPYL BIGUANIDE; .ALPHA.-TOCOPHEROL ACETATE, D-; ANHYDROUS CITRIC ACID; GLYCERIN; PHENOXYETHANOL; WATER

Hanbon ALCOHOL-FREE SANITIZING WIPES
20PCS 40562-010-01

Active Ingredient(s)

Benzalkonium Chloride 0.13mg in 100mL

Purpose

Antibacterial

Use

For hand washing to decrease bacteria on the skin.

Warnings

For external use only.

Do not use

- in the eyes.
- if you are allergic to any of the ingredients.

WHEN USING

If eye contact occurs, rinse thoroughly with water.

STOP USE

If irritation or redness develops and persist for more than 72 hours.

KEEP OUT OF REACH OF CHILDREN

If swallowed, get medical help or contact a Poison Control Center right away.

Directions

- Storage. Store at room temperature.
- Dispensing. Peel back from label. Remove wipe(s). Reseal by pressing label over opening.
- Use. Apply wipe thoroughly to hands as desired. Allow to dry without wiping.
- Disposal. Dispose of used wipes in trash receptacle after use. Do not flush.

Inactive ingredients

Water, Glycerin, Phenoxyethanol, Aloe Barbadensis Leaf Extract, Polysorbate 20, Polyaminopropyl Biguanide, 2-bromo-2-nitropropane-1,3-diol, Tocopheryl Acetate, Citric Acid.

Package Label - Principal Display Panel

20 PATCH in 1 PACKET NDC: 40562-010-01